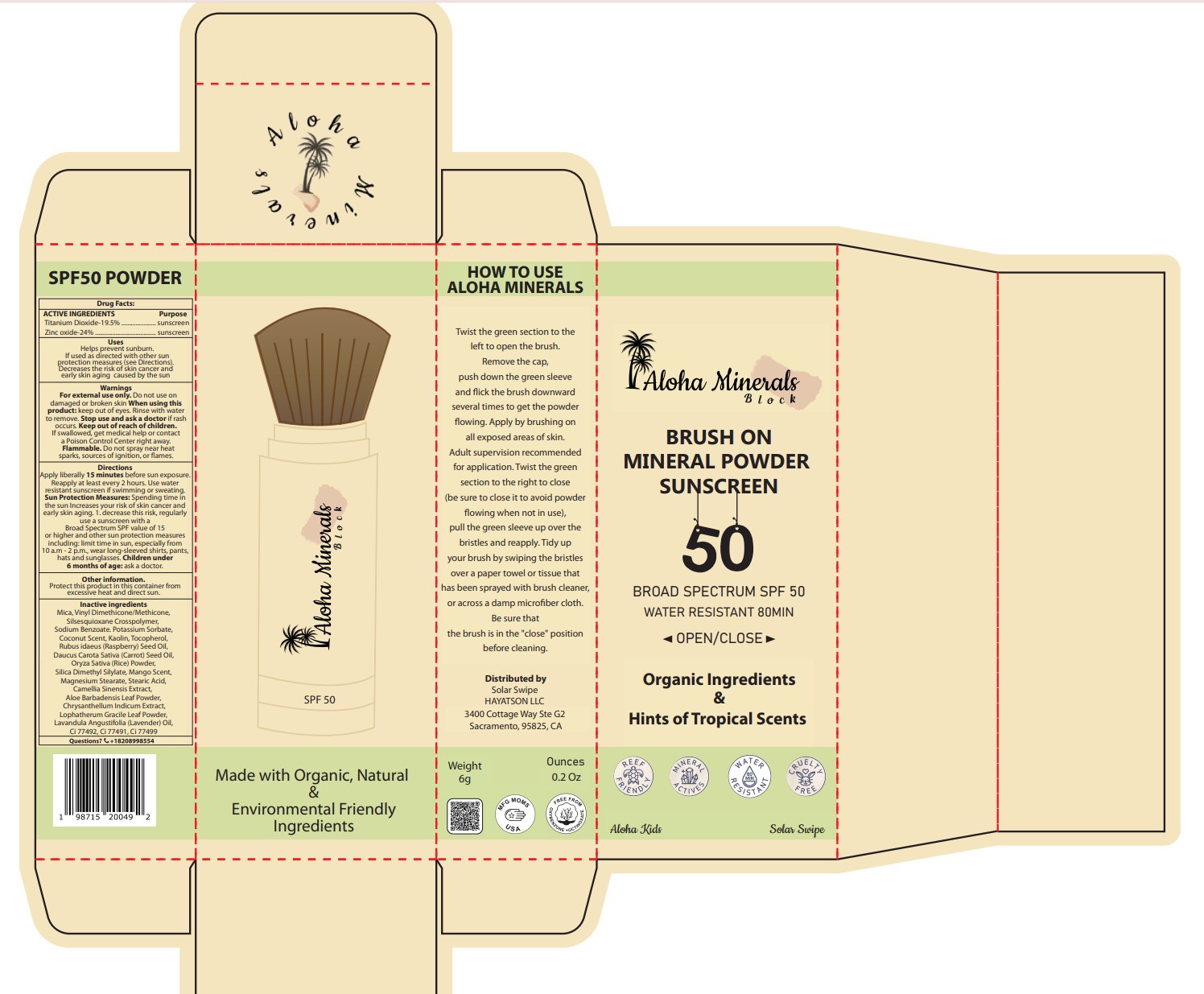 DRUG LABEL: ALOHA MINERAL BLOCK-BRUSH ON MINERAL
NDC: 87283-004 | Form: POWDER
Manufacturer: Aopline Biotechnology (Guangzhou) Co., Ltd.
Category: otc | Type: HUMAN OTC DRUG LABEL
Date: 20260108

ACTIVE INGREDIENTS: TITANIUM DIOXIDE 19.5 g/100 g; ZINC OXIDE 24 g/100 g
INACTIVE INGREDIENTS: SILICA DIMETHYL SILYLATE; MAGNESIUM STEARATE; MICA; RASPBERRY SEED OIL; CHRYSANTHELLUM INDICUM TOP; LAVENDER OIL; STEARIC ACID; COCONUT; POTASSIUM SORBATE; RICE BRAN; FERRIC OXIDE YELLOW; LOPHATHERUM GRACILE LEAF; FERROSOFERRIC OXIDE; TOCOPHEROL; CARROT SEED OIL; GREEN TEA LEAF; FERRIC OXIDE RED; KAOLIN; ALOE VERA LEAF; MANGO; VINYL DIMETHICONE/METHICONE SILSESQUIOXANE CROSSPOLYMER; SODIUM BENZOATE

87283-004-01 ALOHA MINERAL BLOCK-BRUSH ON MINERAL POWDER SUNSCREEN SPF50

ACTIVE INGREDIENT

Titanium dioxide-19.5%

Zinc oxide-24%

PURPOSE

Sunscreen

WARNINGS

Flammable. Do not spray near heat sparks, sources of ignition, or flames.

DOSAGE AND ADMINISTRATION

Apply liberally 15 minutes before sun exposure. Reapply at least every 2 hour

Keep out of reach of children. If swallowed, get medical help or contact a Poison Control Center right away.

When using this product: keep out of eyes. Rinse with water to remove. Stop use and ask a doctor if rash occurs. Keep out of reach of children. If swallowed, get medical help or contact a Poison Control Center right away.

INACTIVE INGREDIENT

Mica, Vinyl Dimethicone/Methicone,Silsesquioxane Crosspolymer, Sodium Benzoate. Potassium Sorbate,Coconut Scent, Kaolin, Tocopherol,Rubus idaeus (Raspberry) Seed Oil, Daucus Carota Sativa (Carrot) Seed Oil,Oryza Sativa (Rice) Powder,Silica Dimethyl Silylate, Mango Scent,Magnesium Stearate, Stearic Acid,Camellia Sinensis Extract, Aloe Barbadensis Leaf Powder,Chrysanthellum Indicum Extract,Lophatherum Gracile Leaf Powder,Lavandula Angustifolia (Lavender) Oil,Ci 77492, Ci 77491, Ci 77499